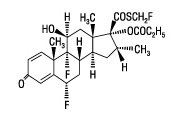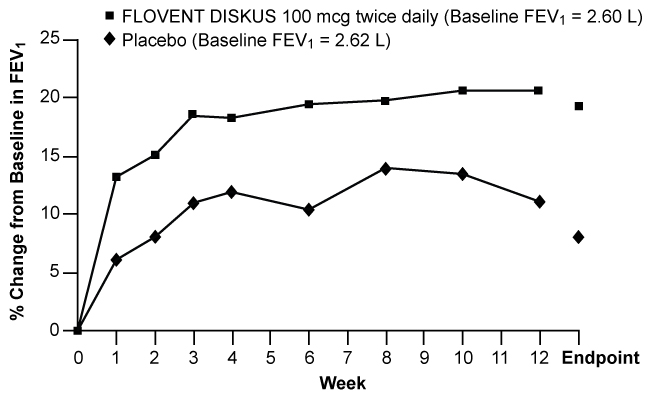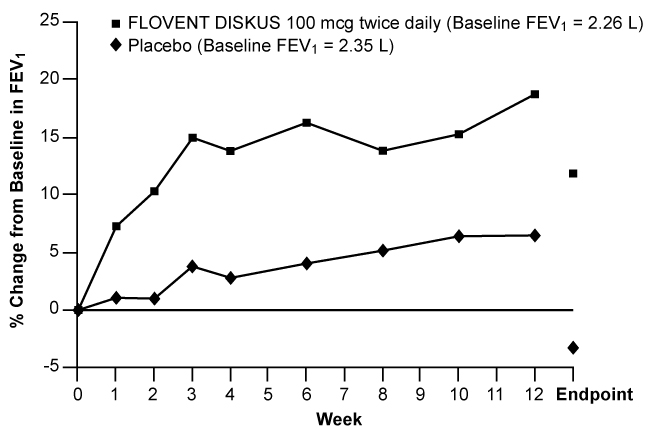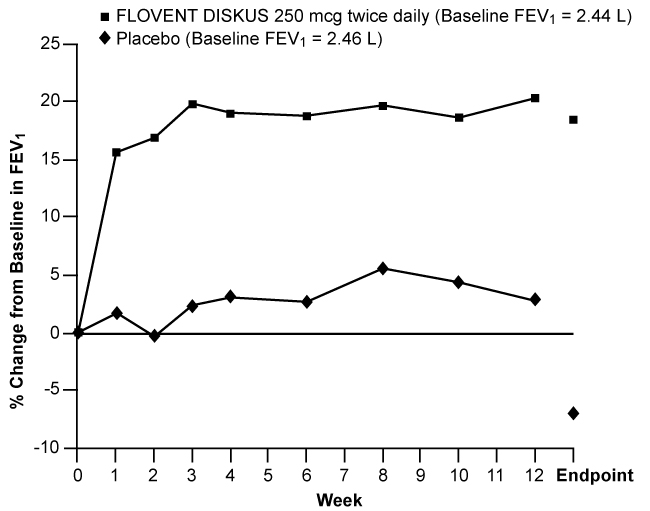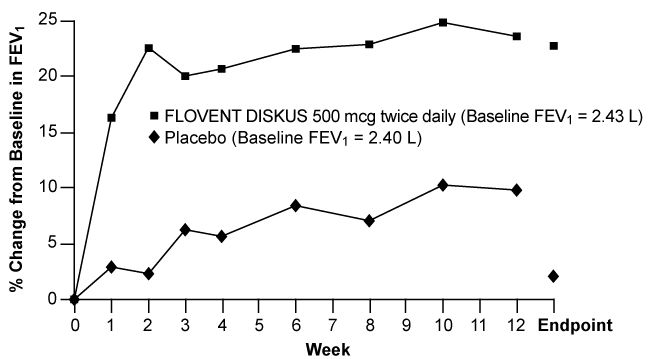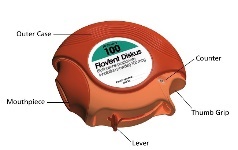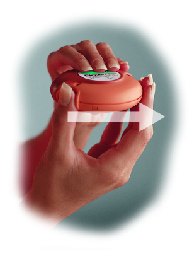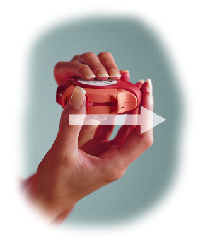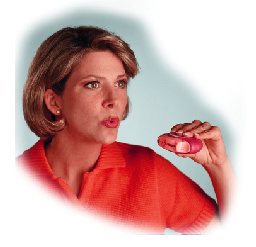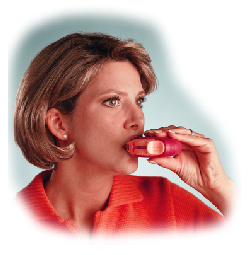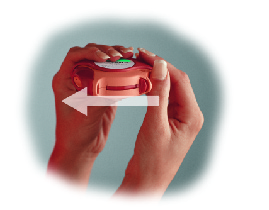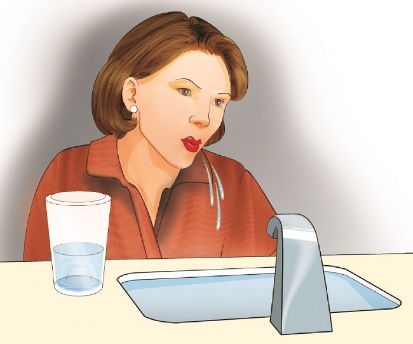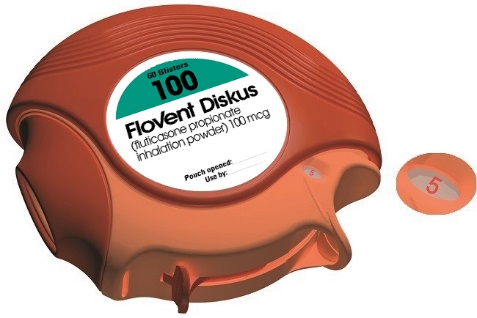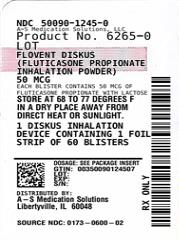 DRUG LABEL: FLOVENT
NDC: 50090-1245 | Form: POWDER, METERED
Manufacturer: A-S Medication Solutions
Category: prescription | Type: HUMAN PRESCRIPTION DRUG LABEL
Date: 20240111

ACTIVE INGREDIENTS: FLUTICASONE PROPIONATE 50 ug/1 1
INACTIVE INGREDIENTS: LACTOSE, UNSPECIFIED FORM

HIGHLIGHTS OF PRESCRIBING INFORMATION

These highlights do not include all the information needed to use FLOVENT DISKUS safely and effectively. See full prescribing information for FLOVENT DISKUS.
FLOVENT DISKUS (fluticasone propionate inhalation powder), for oral inhalation use
Initial U.S. Approval: 1994

1 INDICATIONS AND USAGE

FLOVENT DISKUS is an inhaled corticosteroid (ICS) indicated for:

- Maintenance treatment of asthma as prophylactic therapy in patients aged 4 years and older. (1)

Important limitation:

- Not indicated for relief of acute bronchospasm. (1)

2 DOSAGE AND ADMINISTRATION

- For oral inhalation only. (2.1)
- Starting dosage is based on prior asthma therapy and disease severity. (2.2)
- Treatment of asthma in patients aged 12 years and older: 100 mcg twice daily up to a maximum recommended dosage of 1,000 mcg twice daily. (2.2)
- Treatment of asthma in patients aged 4 to 11 years: 50 mcg twice daily up to a maximum recommended dosage of 100 mcg twice daily. (2.2)

3 DOSAGE FORMS AND STRENGTHS

Inhalation powder: Inhaler containing fluticasone propionate (50, 100, or 250 mcg) as a powder formulation for oral inhalation. (3)

4 CONTRAINDICATIONS

- Primary treatment of status asthmaticus or acute episodes of asthma requiring intensive measures. (4)
- Severe hypersensitivity to milk proteins or demonstrated hypersensitivity to fluticasone propionate. (4)

5 WARNINGS AND PRECAUTIONS

- Candida albicans infection of the mouth and pharynx may occur. Monitor patients periodically. Advise the patient to rinse his/her mouth with water without swallowing after inhalation to help reduce the risk. (5.1)
- Potential worsening of infections (e.g., existing tuberculosis; fungal, bacterial, viral, or parasitic infection; ocular herpes simplex). Use with caution in patients with these infections. More serious or even fatal course of chickenpox or measles can occur in susceptible patients. (5.3)
- Risk of impaired adrenal function when transferring from systemic corticosteroids. Taper patients slowly from systemic corticosteroids if transferring to FLOVENT DISKUS. (5.4)
- Hypercorticism and adrenal suppression may occur with very high dosages or at the regular dosage in susceptible individuals. If such changes occur, discontinue FLOVENT DISKUS slowly. (5.5)
- Assess for decrease in bone mineral density initially and periodically thereafter. (5.7)
- Monitor growth of pediatric patients. (5.8)
- Glaucoma and cataracts may occur with long-term use of ICS. Consider referral to an ophthalmologist in patients who develop ocular symptoms or use FLOVENT DISKUS long term. (5.9)

6 ADVERSE REACTIONS

Most common adverse reactions (incidence >3%) include upper respiratory tract infection or inflammation, throat irritation, sinusitis, rhinitis, oral candidiasis, nausea and vomiting, gastrointestinal discomfort, fever, cough, bronchitis, and headache. (6.1)

To report SUSPECTED ADVERSE REACTIONS, contact GlaxoSmithKline at 1-888-825-5249 or FDA at 1-800-FDA-1088 or www.fda.gov/medwatch.

7 DRUG INTERACTIONS

Strong cytochrome P450 3A4 inhibitors (e.g., ritonavir, ketoconazole): Use not recommended. May increase risk of systemic corticosteroid effects. (7.1)

8 USE IN SPECIFIC POPULATIONS

Hepatic impairment: Monitor patients for signs of increased drug exposure. (8.6)

FULL PRESCRIBING INFORMATION

1 INDICATIONS AND USAGE

FLOVENT DISKUS is indicated for the maintenance treatment of asthma as prophylactic therapy in patients aged 4 years and older.

Important Limitation of Use

FLOVENT DISKUS is NOT indicated for the relief of acute bronchospasm.

2 DOSAGE AND ADMINISTRATION

2.1 Administration Information

FLOVENT DISKUS should be administered by the orally inhaled route in patients aged 4 years and older. After inhalation, the patient should rinse his/her mouth with water without swallowing to help reduce the risk of oropharyngeal candidiasis.

2.2 Recommended Dosage

Adult and Adolescent Patients Aged 12 Years and Older

The starting dosage is based on previous asthma therapy and asthma severity, including consideration of patients’ current control of asthma symptoms and risk of future exacerbation. The recommended starting dosage for patients aged 12 years and older who are not on an inhaled corticosteroid (ICS) is 100 mcg twice daily, approximately 12 hours apart. For other patients, and for patients who do not respond adequately to the starting dosage after 2 weeks of therapy, higher dosages may provide additional asthma control. The maximum recommended dosage for patients aged 12 years and older is 1,000 mcg twice daily.

Pediatric Patients Aged 4 to 11 Years

The starting dosage is based on previous asthma therapy and asthma severity, including consideration of patients’ current control of asthma symptoms and risk of future exacerbation. For patients aged 4 to 11 years not on an ICS, the recommended starting dosage is 50 mcg twice daily, approximately 12 hours apart. For other patients, and for patients who do not respond adequately to the starting dosage after 2 weeks of therapy, increasing the dosage to 100 mcg twice daily may provide additional asthma control. The maximum recommended dosage for patients aged 4 to 11 years is 100 mcg twice daily.

General Dosing Recommendations

If symptoms arise between doses, an inhaled short-acting beta2-agonist should be used for immediate relief.

Individual patients will experience a variable time to onset and degree of symptom relief. Maximum benefit may not be achieved for 1 to 2 weeks or longer after starting treatment.

If a dosage regimen fails to provide adequate control of asthma, the therapeutic regimen should be re-evaluated and additional therapeutic options, e.g., replacing the current strength with a higher strength, initiating an ICS and long-acting beta2-agonist (LABA) combination product, or initiating oral corticosteroids, should be considered.

After asthma stability has been achieved, titrate to the lowest effective dosage to reduce the possibility of side effects.

3 DOSAGE FORMS AND STRENGTHS

Inhalation powder: Inhaler containing a foil blister strip of powder formulation for oral inhalation. The strip contains fluticasone propionate 50, 100, or 250 mcg per blister.

4 CONTRAINDICATIONS

The use of FLOVENT DISKUS is contraindicated in the following conditions:

- Primary treatment of status asthmaticus or other acute episodes of asthma where intensive measures are required [see Warnings and Precautions (5.2)]
- Severe hypersensitivity to milk proteins or demonstrated hypersensitivity to fluticasone propionate [see Warnings and Precautions (5.6), Adverse Reactions (6.2), Description (11)]

5 WARNINGS AND PRECAUTIONS

5.1 Local Effects of Inhaled Corticosteroids

In clinical trials, the development of localized infections of the mouth and pharynx with Candida albicans has occurred in subjects treated with FLOVENT DISKUS. When such an infection develops, it should be treated with appropriate local or systemic (i.e., oral) antifungal therapy while treatment with FLOVENT DISKUS continues, but at times therapy with FLOVENT DISKUS may need to be interrupted. Advise the patient to rinse his/her mouth with water without swallowing following inhalation to help reduce the risk of oropharyngeal candidiasis.

5.2 Acute Asthma Episodes

FLOVENT DISKUS is not to be regarded as a bronchodilator and is not indicated for rapid relief of bronchospasm. Patients should be instructed to contact their physicians immediately when episodes of asthma that are not responsive to bronchodilators occur during the course of treatment with FLOVENT DISKUS. During such episodes, patients may require therapy with oral corticosteroids.

5.3 Immunosuppression

Persons who are using drugs that suppress the immune system are more susceptible to infections than healthy individuals. Chickenpox and measles, for example, can have a more serious or even fatal course in susceptible children or adults using corticosteroids. In such children or adults who have not had these diseases or been properly immunized, particular care should be taken to avoid exposure. How the dose, route, and duration of corticosteroid administration affect the risk of developing a disseminated infection is not known. The contribution of the underlying disease and/or prior corticosteroid treatment to the risk is also not known. If a patient is exposed to chickenpox, prophylaxis with varicella zoster immune globulin (VZIG) may be indicated. If a patient is exposed to measles, prophylaxis with pooled intramuscular immunoglobulin (IG) may be indicated. (See the respective package inserts for complete VZIG and IG prescribing information.) If chickenpox develops, treatment with antiviral agents may be considered.

ICS should be used with caution, if at all, in patients with active or quiescent tuberculosis infections of the respiratory tract; systemic fungal, bacterial, viral, or parasitic infections; or ocular herpes simplex.

5.4 Transferring Patients from Systemic Corticosteroid Therapy

Particular care is needed for patients who have been transferred from systemically active corticosteroids to ICS because deaths due to adrenal insufficiency have occurred in patients with asthma during and after transfer from systemic corticosteroids to less systemically available ICS. After withdrawal from systemic corticosteroids, a number of months are required for recovery of hypothalamic-pituitary-adrenal (HPA) function.

Patients who have been previously maintained on 20 mg or more of prednisone (or its equivalent) may be most susceptible, particularly when their systemic corticosteroids have been almost completely withdrawn. During this period of HPA suppression, patients may exhibit signs and symptoms of adrenal insufficiency when exposed to trauma, surgery, or infection (particularly gastroenteritis) or other conditions associated with severe electrolyte loss. Although FLOVENT DISKUS may control asthma symptoms during these episodes, in recommended doses it supplies less than normal physiological amounts of glucocorticoid systemically and does NOT provide the mineralocorticoid activity that is necessary for coping with these emergencies.

During periods of stress or a severe asthma attack, patients who have been withdrawn from systemic corticosteroids should be instructed to resume oral corticosteroids (in large doses) immediately and to contact their physicians for further instruction. These patients should also be instructed to carry a warning card indicating that they may need supplementary systemic corticosteroids during periods of stress or a severe asthma attack.

Patients requiring oral corticosteroids should be weaned slowly from systemic corticosteroid use after transferring to FLOVENT DISKUS. Prednisone reduction can be accomplished by reducing the daily prednisone dose by 2.5 mg on a weekly basis during therapy with FLOVENT DISKUS. Lung function (mean forced expiratory volume in 1 second [FEV1] or morning peak expiratory flow [AM PEF]), beta-agonist use, and asthma symptoms should be carefully monitored during withdrawal of oral corticosteroids. In addition, patients should be observed for signs and symptoms of adrenal insufficiency, such as fatigue, lassitude, weakness, nausea and vomiting, and hypotension.

Transfer of patients from systemic corticosteroid therapy to FLOVENT DISKUS may unmask allergic conditions previously suppressed by the systemic corticosteroid therapy (e.g., rhinitis, conjunctivitis, eczema, arthritis, eosinophilic conditions).

During withdrawal from oral corticosteroids, some patients may experience symptoms of systemically active corticosteroid withdrawal (e.g., joint and/or muscular pain, lassitude, depression) despite maintenance or even improvement of respiratory function.

5.5 Hypercorticism and Adrenal Suppression

Fluticasone propionate will often help control asthma symptoms with less suppression of HPA function than therapeutically equivalent oral doses of prednisone. Since fluticasone propionate is absorbed into the circulation and can be systemically active at higher doses, the beneficial effects of FLOVENT DISKUS in minimizing HPA dysfunction may be expected only when recommended dosages are not exceeded and individual patients are titrated to the lowest effective dose. A relationship between plasma levels of fluticasone propionate and inhibitory effects on stimulated cortisol production has been shown after 4 weeks of treatment with fluticasone propionate inhalation aerosol. Since individual sensitivity to effects on cortisol production exists, physicians should consider this information when prescribing FLOVENT DISKUS.

Because of the possibility of significant systemic absorption of ICS in sensitive patients, patients treated with FLOVENT DISKUS should be observed carefully for any evidence of systemic corticosteroid effects. Particular care should be taken in observing patients postoperatively or during periods of stress for evidence of inadequate adrenal response.

It is possible that systemic corticosteroid effects such as hypercorticism and adrenal suppression (including adrenal crisis) may appear in a small number of patients who are sensitive to these effects. If such effects occur, FLOVENT DISKUS should be reduced slowly, consistent with accepted procedures for reducing systemic corticosteroids, and other treatments for management of asthma symptoms should be considered.

5.6 Immediate Hypersensitivity Reactions

Immediate hypersensitivity reactions (e.g., urticaria, angioedema, rash, bronchospasm, hypotension), including anaphylaxis, may occur after administration of FLOVENT DISKUS. There have been reports of anaphylactic reactions in patients with severe milk protein allergy after inhalation of powder products containing lactose; therefore, patients with severe milk protein allergy should not use FLOVENT DISKUS [see Contraindications (4)].

5.7 Reduction in Bone Mineral Density

Decreases in bone mineral density (BMD) have been observed with long-term administration of products containing ICS. The clinical significance of small changes in BMD with regard to long-term consequences such as fracture is unknown. Patients with major risk factors for decreased bone mineral content, such as prolonged immobilization, family history of osteoporosis, postmenopausal status, tobacco use, advanced age, poor nutrition, or chronic use of drugs that can reduce bone mass (e.g., anticonvulsants, oral corticosteroids), should be monitored and treated with established standards of care.

A 2-year trial in 160 subjects (females aged 18 to 40 years, males 18 to 50) with asthma receiving chlorofluorocarbon (CFC)-propelled fluticasone propionate inhalation aerosol 88 or 440 mcg twice daily demonstrated no statistically significant changes in BMD at any time point (24, 52, 76, and 104 weeks of double-blind treatment) as assessed by dual-energy x-ray absorptiometry at lumbar regions L1 through L4.

5.8 Effect on Growth

Orally inhaled corticosteroids may cause a reduction in growth velocity when administered to pediatric patients. Monitor the growth of pediatric patients receiving FLOVENT DISKUS routinely (e.g., via stadiometry). To minimize the systemic effects of orally inhaled corticosteroids, including FLOVENT DISKUS, titrate each patient’s dosage to the lowest dosage that effectively controls his/her symptoms [see Dosage and Administration (2.2), Use in Specific Populations (8.4)].

5.9 Glaucoma and Cataracts

Glaucoma, increased intraocular pressure, and cataracts have been reported in patients following the long-term administration of ICS, including fluticasone propionate. Consider referral to an ophthalmologist in patients who develop ocular symptoms or use FLOVENT DISKUS long term.

5.10 Paradoxical Bronchospasm

As with other inhaled medicines, bronchospasm may occur with an immediate increase in wheezing after dosing. If bronchospasm occurs following dosing with FLOVENT DISKUS, it should be treated immediately with an inhaled, short-acting bronchodilator; FLOVENT DISKUS should be discontinued immediately; and alternative therapy should be instituted.

5.11 Drug Interactions with Strong Cytochrome P450 3A4 Inhibitors

The use of strong cytochrome P450 3A4 (CYP3A4) inhibitors (e.g., ritonavir, atazanavir, clarithromycin, indinavir, itraconazole, nefazodone, nelfinavir, saquinavir, ketoconazole, telithromycin) with FLOVENT DISKUS is not recommended because increased systemic corticosteroid adverse effects may occur [see Drug Interactions (7.1), Clinical Pharmacology (12.3)].

5.12 Eosinophilic Conditions and Churg-Strauss Syndrome

In rare cases, patients on inhaled fluticasone propionate may present with systemic eosinophilic conditions. Some of these patients have clinical features of vasculitis consistent with Churg-Strauss syndrome, a condition that is often treated with systemic corticosteroid therapy. These events usually, but not always, have been associated with the reduction and/or withdrawal of oral corticosteroid therapy following the introduction of fluticasone propionate. Cases of serious eosinophilic conditions have also been reported with other ICS in this clinical setting. Physicians should be alert to eosinophilia, vasculitic rash, worsening pulmonary symptoms, cardiac complications, and/or neuropathy presenting in their patients. A causal relationship between fluticasone propionate and these underlying conditions has not been established.

6 ADVERSE REACTIONS

Systemic and local corticosteroid use may result in the following:

- Candida albicans infection [see Warnings and Precautions (5.1)]
- Immunosuppression [see Warnings and Precautions (5.3)]
- Hypercorticism and adrenal suppression [see Warnings and Precautions (5.5)]
- Reduction in bone mineral density [see Warnings and Precautions (5.7)]
- Growth effects [see Warnings and Precautions (5.8)]
- Glaucoma and cataracts [see Warnings and Precautions (5.9)]

6.1 Clinical Trials Experience

Because clinical trials are conducted under widely varying conditions, adverse reaction rates observed in the clinical trials of a drug cannot be directly compared with rates in the clinical trials of another drug and may not reflect the rates observed in practice.

The incidence of common adverse reactions in Table 1 is based upon 7 placebo-controlled U.S. clinical trials in which 1,176 pediatric, adolescent, and adult subjects (466 females and 710 males) previously treated with as-needed bronchodilators and/or ICS were treated twice daily for up to 12 weeks with FLOVENT DISKUS (doses of 50 to 500 mcg) or placebo.

Table 1. Adverse Reactions with FLOVENT DISKUS with >3% Incidence and More Common than Placebo in Subjects with Asthma

Adverse Event | FLOVENT DISKUS 50 mcg; Twice Daily; (n = 178); % | FLOVENT DISKUS 100 mcg; Twice Daily; (n = 305); % | FLOVENT DISKUS 250 mcg; Twice Daily; (n = 86); % | FLOVENT DISKUS 500 mcg; Twice Daily; (n = 64); % | Placebo; (n = 543); %
Ear, nose, and throat
Upper respiratory tract infection | 20 | 18 | 21 | 14 | 16
Throat irritation | 13 | 13 | 3 | 22 | 8
Sinusitis/sinus infection | 9 | 10 | 6 | 6 | 6
Upper respiratory inflammation | 5 | 5 | 0 | 5 | 3
Rhinitis | 4 | 3 | 1 | 2 | 2
Oral candidiasis | <1 | 9 | 6 | 5 | 7
Gastrointestinal
Nausea and vomiting | 8 | 4 | 1 | 2 | 4
Gastrointestinal discomfort and pain | 4 | 3 | 2 | 2 | 3
Viral gastrointestinal infection | 4 | 3 | 3 | 5 | 1
Non-site specific
Fever | 7 | 7 | 1 | 2 | 4
Viral infection | 2 | 2 | 0 | 5 | 2
Lower respiratory
Viral respiratory infection | 4 | 5 | 1 | 2 | 4
Cough | 3 | 5 | 1 | 5 | 4
Bronchitis | 2 | 3 | 0 | 8 | 1
Neurological
Headache | 12 | 12 | 2 | 14 | 7
Musculoskeletal and trauma
Muscle injury | 2 | 0 | 1 | 5 | 1
Musculoskeletal pain | 4 | 3 | 2 | 5 | 2
Injury | 2 | <1 | 0 | 5 | <1

Table 1 includes all events (whether considered drug-related or nondrug-related by the investigator) that occurred at a rate of over 3% in any of the groups treated with FLOVENT DISKUS and were more common than in the placebo group. Less than 2% of subjects discontinued from the trials because of adverse reactions. The average duration of exposure was 73 to 79 days in the active treatment groups compared with 56 days in the placebo group.

Additional Adverse Reactions

Other adverse reactions not previously listed, whether considered drug-related or not by the investigators, that were reported more frequently by subjects with asthma treated with FLOVENT DISKUS compared with subjects treated with placebo include the following: palpitations; soft tissue injuries; contusions and hematomas; wounds and lacerations; burns; poisoning and toxicity; pressure-induced disorders; hoarseness/dysphonia; epistaxis; ear, nose, throat, and tonsil signs and symptoms; ear, nose, and throat polyps; allergic ear, nose, and throat disorders; throat constriction; fluid disturbances; weight gain; appetite disturbances; keratitis and conjunctivitis; blepharoconjunctivitis; gastrointestinal signs and symptoms; oral ulcerations; dental discomfort and pain; oral erythema and rashes; mouth and tongue disorders; oral discomfort and pain; tooth decay; cholecystitis; arthralgia and articular rheumatism; muscle cramps and spasms; musculoskeletal inflammation; dizziness; sleep disorders; migraines; paralysis of cranial nerves; edema and swelling; bacterial infections; fungal infections; mobility disorders; mood disorders; bacterial reproductive infections; photodermatitis; dermatitis and dermatosis; viral skin infections; eczema; pruritus; acne and folliculitis; urinary infections.

Three (3) of the 7 placebo-controlled U.S. clinical trials were pediatric trials. A total of 592 subjects aged 4 to 11 years were treated with FLOVENT DISKUS (dosages of 50 or 100 mcg twice daily) or placebo; an additional 174 subjects aged 4 to 11 years received FLOVENT ROTADISK (fluticasone propionate inhalation powder) at the same doses. There were no clinically relevant differences in the pattern or severity of adverse events in children compared with those reported in adults.

In the first 16 weeks of a 52-week clinical trial in adult subjects with asthma who previously required oral corticosteroids (daily doses of 5 to 40 mg oral prednisone), the effects of FLOVENT DISKUS 500 mcg twice daily (n = 41) and 1,000 mcg twice daily (n = 36) were compared with placebo (n = 34) for the frequency of reported adverse events. The average duration of exposure for subjects taking FLOVENT DISKUS was 105 days compared with 75 days for placebo. Adverse events, whether or not considered drug related by the investigators, reported in more than 5 subjects in the group taking FLOVENT DISKUS and that occurred more frequently with FLOVENT DISKUS than with placebo are shown below (percent FLOVENT DISKUS and percent placebo).

Ear, Nose, and Throat: Hoarseness/dysphonia (9% and 0%), nasal congestion/blockage (16% and 0%), oral candidiasis (31% and 21%), rhinitis (13% and 9%), sinusitis/sinus infection (33% and 12%), throat irritation (10% and 9%), and upper respiratory tract infection (31% and 24%).

Gastrointestinal: Nausea and vomiting (9% and 0%).

Lower Respiratory: Cough (9% and 3%) and viral respiratory infections (9% and 6%).

Musculoskeletal: Arthralgia and articular rheumatism (17% and 3%) and muscle pain (12% and 0%).

Non-Site Specific: Malaise and fatigue (16% and 9%) and pain (10% and 3%).

Skin: Pruritus (6% and 0%) and skin rashes (8% and 3%).

6.2 Postmarketing Experience

In addition to adverse reactions reported from clinical trials, the following adverse reactions have been identified during postapproval use of fluticasone propionate. Because these reactions are reported voluntarily from a population of uncertain size, it is not always possible to reliably estimate their frequency or establish a causal relationship to drug exposure. These events have been chosen for inclusion due to either their seriousness, frequency of reporting, or causal connection to fluticasone propionate or a combination of these factors.

Ear, Nose, and Throat

Aphonia, facial and oropharyngeal edema, and throat soreness.

Endocrine and Metabolic

Cushingoid features, growth velocity reduction in children/adolescents, hyperglycemia, and osteoporosis.

Eye

Cataracts.

Immune System Disorders

Immediate and delayed hypersensitivity reactions, including anaphylaxis, rash, angioedema, and bronchospasm, have been reported. Anaphylactic reactions in patients with severe milk protein allergy have been reported.

Infections and Infestations

Esophageal candidiasis.

Psychiatry

Agitation, aggression, anxiety, depression, and restlessness. Behavioral changes, including hyperactivity and irritability, have been reported very rarely and primarily in children.

Respiratory

Asthma exacerbation, bronchospasm, chest tightness, dyspnea, immediate bronchospasm, pneumonia, and wheeze.

Skin

Contusions and ecchymoses.

7 DRUG INTERACTIONS

7.1 Inhibitors of Cytochrome P450 3A4

Fluticasone propionate is a substrate of CYP3A4. The use of strong CYP3A4 inhibitors (e.g., ritonavir, atazanavir, clarithromycin, indinavir, itraconazole, nefazodone, nelfinavir, saquinavir, ketoconazole, telithromycin) with FLOVENT DISKUS is not recommended because increased systemic corticosteroid adverse effects may occur.

Ritonavir

A drug interaction trial with fluticasone propionate aqueous nasal spray in healthy subjects has shown that ritonavir (a strong CYP3A4 inhibitor) can significantly increase plasma fluticasone propionate exposure, resulting in significantly reduced serum cortisol concentrations [see Clinical Pharmacology (12.3)]. During postmarketing use, there have been reports of clinically significant drug interactions in patients receiving fluticasone propionate and ritonavir, resulting in systemic corticosteroid effects including Cushing’s syndrome and adrenal suppression.

Ketoconazole

Coadministration of orally inhaled fluticasone propionate (1,000 mcg) and ketoconazole (200 mg once daily) resulted in a 1.9-fold increase in plasma fluticasone propionate exposure and a 45% decrease in plasma cortisol area under the curve (AUC), but had no effect on urinary excretion of cortisol.

8 USE IN SPECIFIC POPULATIONS

8.1 Pregnancy

Risk Summary

There are insufficient data on the use of FLOVENT DISKUS in pregnant women. There are clinical considerations with the use of FLOVENT DISKUS in pregnant women. (See Clinical Considerations.) In animals, teratogenicity characteristic of corticosteroids, decreased fetal body weight, and/or skeletal variations in rats, mice, and rabbits were observed with subcutaneously administered maternal toxic doses of fluticasone propionate less than the maximum recommended human daily inhaled dose (MRHDID) on a mcg/m^2 basis. (See Data.) However, fluticasone propionate administered via inhalation to rats decreased fetal body weight, but did not induce teratogenicity at a maternal toxic dose less than the MRHDID on a mcg/m^2 basis. (See Data.) Experience with oral corticosteroids suggests that rodents are more prone to teratogenic effects from corticosteroids than humans.

The estimated risk of major birth defects and miscarriage for the indicated population is unknown. In the U.S. general population, the estimated risk of major birth defects and miscarriage in clinically recognized pregnancies is 2% to 4% and 15% to 20%, respectively.

Clinical Considerations

Disease-Associated Maternal and/or Embryofetal Risk: In women with poorly or moderately controlled asthma, there is an increased risk of several perinatal outcomes such as pre-eclampsia in the mother and prematurity, low birth weight, and small for gestational age in the neonate. Pregnant women with asthma should be closely monitored and medication adjusted as necessary to maintain optimal asthma control.

Data

Human Data: Following inhaled administration, fluticasone propionate was detected in the neonatal cord blood after delivery.

Animal Data: In embryofetal development studies with pregnant rats and mice dosed by the subcutaneous route throughout the period of organogenesis, fluticasone propionate was teratogenic in both species. Omphalocele, decreased body weight, and skeletal variations were observed in rat fetuses, in the presence of maternal toxicity, at a dose approximately 0.5 times the MRHDID (on a mcg/m^2 basis with a maternal subcutaneous dose of 100 mcg/kg/day). The rat no observed adverse effect level (NOAEL) was observed at approximately 0.15 times the MRHDID (on a mcg/m^2 basis with a maternal subcutaneous dose of 30 mcg/kg/day). Cleft palate and fetal skeletal variations were observed in mouse fetuses at a dose approximately 0.1 times the MRHDID (on a mcg/m^2 basis with a maternal subcutaneous dose of 45 mcg/kg/day). The mouse NOAEL was observed with a dose approximately 0.04 times the MRHDID (on a mcg/m^2 basis with a maternal subcutaneous dose of 15 mcg/kg/day).

In an embryofetal development study with pregnant rats dosed by the inhalation route throughout the period of organogenesis, fluticasone propionate produced decreased fetal body weights and skeletal variations, in the presence of maternal toxicity, at a dose approximately 0.13 times the MRHDID (on a mcg/m^2 basis with a maternal inhalation dose of 25.7 mcg/kg/day); however, there was no evidence of teratogenicity. The NOAEL was observed with a dose approximately 0.03 times the MRHDID (on a mcg/m^2 basis with a maternal inhalation dose of 5.5 mcg/kg/day).

In an embryofetal development study in pregnant rabbits that were dosed by the subcutaneous route throughout organogenesis, fluticasone propionate produced reductions of fetal body weights, in the presence of maternal toxicity, at doses approximately 0.006 times the MRHDID and higher (on a mcg/m^2 basis with a maternal subcutaneous dose of 0.57 mcg/kg/day). Teratogenicity was evident based upon a finding of cleft palate for 1 fetus at a dose approximately 0.04 times the MRHDID (on a mcg/m^2 basis with a maternal subcutaneous dose of 4 mcg/kg/day). The NOAEL was observed in rabbit fetuses with a dose approximately 0.001 times the MRHDID (on a mcg/m^2 basis with a maternal subcutaneous dose of 0.08 mcg/kg/day).

Fluticasone propionate crossed the placenta following subcutaneous administration to mice and rats and oral administration to rabbits.

In a pre- and post-natal development study in pregnant rats dosed from late gestation through delivery and lactation (Gestation Day 17 to Postpartum Day 22), fluticasone propionate was not associated with decreases in pup body weight, and had no effects on developmental landmarks, learning, memory, reflexes, or fertility at doses up to 0.2 times the MRHDID (on a mcg/m^2 basis with maternal subcutaneous doses up to 50 mcg/kg/day).

8.2 Lactation

Risk Summary

There are no available data on the presence of fluticasone propionate in human milk, the effects on the breastfed child, or the effects on milk production. Other corticosteroids have been detected in human milk. However, fluticasone propionate concentrations in plasma after inhaled therapeutic doses are low and therefore concentrations in human breast milk are likely to be correspondingly low [see Clinical Pharmacology (12.3)]. The developmental and health benefits of breastfeeding should be considered along with the mother’s clinical need for FLOVENT DISKUS and any potential adverse effects on the breastfed child from FLOVENT DISKUS or from the underlying maternal condition.

Data

Animal Data: Subcutaneous administration of tritiated fluticasone propionate at a dose of 10 mcg/kg/day to lactating rats resulted in measurable levels in milk.

8.4 Pediatric Use

The safety and effectiveness of FLOVENT DISKUS in children aged 4 years and older have been established [see Adverse Reactions (6.1), Clinical Pharmacology (12.3), Clinical Studies (14.2)]. The safety and effectiveness of FLOVENT DISKUS in children younger than 4 years have not been established.

Effects on Growth

Orally inhaled corticosteroids may cause a reduction in growth velocity when administered to pediatric patients. A reduction of growth velocity in children or teenagers may occur as a result of poorly controlled asthma or from use of corticosteroids, including ICS. The effects of long-term treatment of children and adolescents with ICS, including fluticasone propionate, on final adult height are not known.

Controlled clinical trials have shown that ICS may cause a reduction in growth in pediatric patients. In these trials, the mean reduction in growth velocity was approximately 1 cm/year (range: 0.3 to 1.8 cm/year) and appeared to depend upon dose and duration of exposure. This effect was observed in the absence of laboratory evidence of HPA axis suppression, suggesting that growth velocity is a more sensitive indicator of systemic corticosteroid exposure in pediatric patients than some commonly used tests of HPA axis function. The long‑term effects of this reduction in growth velocity associated with orally inhaled corticosteroids, including the impact on final adult height, are unknown. The potential for “catch-up” growth following discontinuation of treatment with orally inhaled corticosteroids has not been adequately studied. The effects on growth velocity of treatment with orally inhaled corticosteroids for over 1 year, including the impact on final adult height, are unknown. The growth of children and adolescents receiving orally inhaled corticosteroids, including FLOVENT DISKUS, should be monitored routinely (e.g., via stadiometry). The potential growth effects of prolonged treatment should be weighed against the clinical benefits obtained and the risks associated with alternative therapies. To minimize the systemic effects of orally inhaled corticosteroids, including FLOVENT DISKUS, each patient should be titrated to the lowest dose that effectively controls his/her symptoms.

A 52-week placebo-controlled trial to assess the potential growth effects of fluticasone propionate inhalation powder (FLOVENT ROTADISK) at 50 and 100 mcg twice daily was conducted in the U.S. in 325 prepubescent children (244 males and 81 females) aged 4 to 11 years. The mean growth velocities at 52 weeks observed in the intent-to-treat population were 6.32 cm/year in the placebo group (n = 76), 6.07 cm/year in the 50-mcg group (n = 98), and 5.66 cm/year in the 100‑mcg group (n = 89). An imbalance in the proportion of children entering puberty between groups and a higher dropout rate in the placebo group due to poorly controlled asthma may be confounding factors in interpreting these data. A separate subset analysis of children who remained prepubertal during the trial revealed growth rates at 52 weeks of 6.10 cm/year in the placebo group (n = 57), 5.91 cm/year in the 50-mcg group (n = 74), and 5.67 cm/year in the 100‑mcg group (n = 79). In children aged 8.5 years, the mean age of children in this trial, the range for expected growth velocity is: boys – 3rd percentile = 3.8 cm/year, 50th percentile = 5.4 cm/year, and 97th percentile = 7.0 cm/year; girls – 3rd percentile = 4.2 cm/year, 50th percentile = 5.7 cm/year, and 97th percentile = 7.3 cm/year. The clinical relevance of these growth data is not certain.

8.5 Geriatric Use

Safety data have been collected on 280 subjects (FLOVENT DISKUS n = 83, FLOVENT ROTADISK n = 197) aged 65 years and older and 33 subjects (FLOVENT DISKUS n = 14, FLOVENT ROTADISK n = 19) aged 75 years and older who have been treated with fluticasone propionate inhalation powder in U.S. and non-U.S. clinical trials. No overall differences in safety or effectiveness were observed between these subjects and younger subjects, and other reported clinical experience has not identified differences in responses between the elderly and younger subjects, but greater sensitivity of some older individuals cannot be ruled out.

8.6 Hepatic Impairment

Formal pharmacokinetic studies using FLOVENT DISKUS have not been conducted in patients with hepatic impairment. Since fluticasone propionate is predominantly cleared by hepatic metabolism, impairment of liver function may lead to accumulation of fluticasone propionate in plasma. Therefore, patients with hepatic disease should be closely monitored.

8.7 Renal Impairment

Formal pharmacokinetic studies using FLOVENT DISKUS have not been conducted in patients with renal impairment.

10 OVERDOSAGE

Chronic overdosage may result in signs/symptoms of hypercorticism [see Warnings and Precautions (5.5)]. Inhalation by healthy volunteers of a single dose of 4,000 mcg of fluticasone propionate inhalation powder or single doses of 1,760 or 3,520 mcg of fluticasone propionate CFC inhalation aerosol was well tolerated. Fluticasone propionate given by inhalation aerosol at dosages of 1,320 mcg twice daily for 7 to 15 days to healthy human volunteers was also well tolerated. Repeat oral doses up to 80 mg daily for 10 days in healthy volunteers and repeat oral doses up to 20 mg daily for 42 days in subjects were well tolerated. Adverse reactions were of mild or moderate severity, and incidences were similar in active and placebo treatment groups.

11 DESCRIPTION

FLOVENT DISKUS inhalation powder is a dry powder inhaler for oral inhalation. The active component of FLOVENT DISKUS 50 mcg, FLOVENT DISKUS 100 mcg, and FLOVENT DISKUS 250 mcg is fluticasone propionate, a corticosteroid having the chemical name S-(fluoromethyl) 6α,9-difluoro-11β,17-dihydroxy-16α-methyl-3-oxoandrosta-1,4-diene-17β-carbothioate, 17-propionate and the following chemical structure:

Fluticasone propionate is a white powder with a molecular weight of 500.6, and the empirical formula is C25H31F3O5S. It is practically insoluble in water, freely soluble in dimethyl sulfoxide and dimethylformamide, and slightly soluble in methanol and 95% ethanol.

FLOVENT DISKUS is an orange plastic inhaler containing a foil blister strip. Each blister on the strip contains a white powder mix of micronized fluticasone propionate (50, 100, or 250 mcg) in 12.5 mg of formulation containing lactose monohydrate (which contains milk proteins). After the inhaler is activated, the powder is dispersed into the airstream created by the patient inhaling through the mouthpiece.

Under standardized in vitro test conditions, FLOVENT DISKUS delivers 46, 94, and 229 mcg of fluticasone propionate from FLOVENT DISKUS 50 mcg, FLOVENT DISKUS 100 mcg, and FLOVENT DISKUS 250 mcg, respectively, when tested at a flow rate of 60 L/min for 2 seconds.

In adult subjects with obstructive lung disease and severely compromised lung function (mean FEV1 20% to 30% of predicted), mean peak inspiratory flow (PIF) through the DISKUS inhaler was 82.4 L/min (range: 46.1 to 115.3 L/min). In children with asthma aged 4 and 8 years, mean PIF through FLOVENT DISKUS was 70 and 104 L/min, respectively (range: 48 to 123 L/min).

The actual amount of drug delivered to the lung will depend on patient factors, such as inspiratory flow profile.

12 CLINICAL PHARMACOLOGY

12.1 Mechanism of Action

Fluticasone propionate is a synthetic trifluorinated corticosteroid with anti-inflammatory activity. Fluticasone propionate has been shown in vitro to exhibit a binding affinity for the human glucocorticoid receptor that is 18 times that of dexamethasone, almost twice that of beclomethasone-17-monopropionate (BMP), the active metabolite of beclomethasone dipropionate, and over 3 times that of budesonide. Data from the McKenzie vasoconstrictor assay in man are consistent with these results. The clinical significance of these findings is unknown.

Inflammation is an important component in the pathogenesis of asthma. Corticosteroids have been shown to have a wide range of actions on multiple cell types (e.g., mast cells, eosinophils, neutrophils, macrophages, lymphocytes) and mediators (e.g., histamine, eicosanoids, leukotrienes, cytokines) involved in inflammation. These anti-inflammatory actions of corticosteroids contribute to their efficacy in asthma.

Though effective for the treatment of asthma, corticosteroids do not affect asthma symptoms immediately. Individual patients will experience a variable time to onset and degree of symptom relief. Maximum benefit may not be achieved for 1 to 2 weeks or longer after starting treatment. When corticosteroids are discontinued, asthma stability may persist for several days or longer.

Trials in subjects with asthma have shown a favorable ratio between topical anti-inflammatory activity and systemic corticosteroid effects with recommended doses of orally inhaled fluticasone propionate. This is explained by a combination of a relatively high local anti-inflammatory effect, negligible oral systemic bioavailability (<1%), and the minimal pharmacological activity of the only metabolite detected in man.

12.2 Pharmacodynamics

In clinical trials with fluticasone propionate inhalation powder using dosages up to and including 250 mcg twice daily, occasional abnormal short cosyntropin tests (peak serum cortisol <18 mcg/dL assessed by radioimmunoassay) were noted both in subjects receiving fluticasone propionate and in subjects receiving placebo. The incidence of abnormal tests at 500 mcg twice daily was greater than placebo. In a 2-year trial carried out with the DISKHALER inhalation device in 64 subjects with mild, persistent asthma (mean FEV1 91% of predicted) randomized to fluticasone propionate 500 mcg twice daily or placebo, no subject receiving fluticasone propionate had an abnormal response to 6-hour cosyntropin infusion (peak serum cortisol <18 mcg/dL). With a peak cortisol threshold of <35 mcg/dL, 1 subject receiving fluticasone propionate (4%) had an abnormal response at 1 year; repeat testing at 18 months and 2 years was normal. Another subject receiving fluticasone propionate (5%) had an abnormal response at 2 years. No subject on placebo had an abnormal response at 1 or 2 years.

In a placebo-controlled clinical trial conducted in subjects aged 4 to 11 years, a 30-minute cosyntropin stimulation test was performed in 41 subjects after 12 weeks of dosing with 50 or 100 mcg twice daily of fluticasone propionate via the DISKUS inhaler. One subject receiving fluticasone propionate via the DISKUS inhaler had a prestimulation plasma cortisol concentration <5 mcg/dL, and 2 subjects had a rise in cortisol of <7 mcg/dL. However, all poststimulation values were >18 mcg/dL.

The potential systemic effects of inhaled fluticasone propionate on the HPA axis were also studied in subjects with asthma. Fluticasone propionate given by inhalation aerosol at dosages of 220, 440, 660, or 880 mcg twice daily was compared with placebo or oral prednisone 10 mg given once daily for 4 weeks. For most subjects, the ability to increase cortisol production in response to stress, as assessed by 6-hour cosyntropin stimulation, remained intact with inhaled fluticasone propionate treatment. No subject had an abnormal response (peak serum cortisol <18 mcg/dL) after dosing with placebo or fluticasone propionate 220 mcg twice daily. For subjects treated with 440, 660, and 880 mcg twice daily, 10%, 16%, and 12%, respectively, had an abnormal response as compared with 29% of subjects treated with prednisone.

12.3 Pharmacokinetics

Absorption

Fluticasone propionate acts locally in the lung; therefore, plasma levels do not predict therapeutic effect. Trials using oral dosing of labeled and unlabeled drug have demonstrated that the oral systemic bioavailability of fluticasone propionate is negligible (<1%), primarily due to incomplete absorption and presystemic metabolism in the gut and liver. In contrast, the majority of the fluticasone propionate delivered to the lung is systemically absorbed. The absolute bioavailability of fluticasone propionate from the DISKUS inhaler in healthy volunteers averages 7.8%.

Peak steady-state fluticasone propionate plasma concentrations in adult subjects with asthma (N = 11) ranged from undetectable to 266 pg/mL after a 500-mcg twice-daily dose of fluticasone propionate inhalation powder using the DISKUS inhaler. The mean fluticasone propionate plasma concentration was 110 pg/mL.

Distribution

Following intravenous administration, the initial disposition phase for fluticasone propionate was rapid and consistent with its high lipid solubility and tissue binding. The volume of distribution averaged 4.2 L/kg.

The percentage of fluticasone propionate bound to human plasma proteins averages 99%. Fluticasone propionate is weakly and reversibly bound to erythrocytes and is not significantly bound to human transcortin.

Metabolism

The total clearance of fluticasone propionate is high (average, 1,093 mL/min), with renal clearance accounting for <0.02% of the total. The only circulating metabolite detected in man is the 17β-carboxylic acid derivative of fluticasone propionate, which is formed through the CYP3A4 pathway. This metabolite had less affinity (approximately 1/2,000) than the parent drug for the glucocorticoid receptor of human lung cytosol in vitro and negligible pharmacological activity in animal studies. Other metabolites detected in vitro using cultured human hepatoma cells have not been detected in man.

Elimination

Following intravenous dosing, fluticasone propionate showed polyexponential kinetics and had a terminal elimination half-life of approximately 7.8 hours. Less than 5% of a radiolabeled oral dose was excreted in the urine as metabolites, with the remainder excreted in the feces as parent drug and metabolites.

Specific Populations

Male and Female Patients: Full pharmacokinetic profiles were obtained from 9 female and 16 male subjects given 500 mcg twice daily. No overall differences in fluticasone propionate pharmacokinetics were observed.

Pediatric Patients: In a clinical trial conducted in subjects aged 4 to 11 years with mild to moderate asthma, fluticasone propionate concentrations were obtained in 61 subjects at 20 and 40 minutes after dosing with 50 and 100 mcg twice daily of fluticasone propionate inhalation powder using the DISKUS. Plasma concentrations were low and ranged from undetectable (about 80% of the plasma samples) to 88 pg/mL. Mean peak fluticasone propionate plasma concentrations at the 50- and 100-mcg dose levels were 5 and 8 pg/mL, respectively.

Patients with Hepatic and Renal Impairment: Formal pharmacokinetic studies using FLOVENT DISKUS have not been conducted in patients with hepatic or renal impairment. However, since fluticasone propionate is predominantly cleared by hepatic metabolism, impairment of liver function may lead to accumulation of fluticasone propionate in plasma. Therefore, patients with hepatic disease should be closely monitored.

Drug Interaction Studies

Inhibitors of Cytochrome P450 3A4: Ritonavir: Fluticasone propionate is a substrate of CYP3A4. Coadministration of fluticasone propionate and the strong CYP3A4 inhibitor ritonavir is not recommended based upon a multiple-dose, crossover drug interaction trial in 18 healthy subjects. Fluticasone propionate aqueous nasal spray (200 mcg once daily) was coadministered for 7 days with ritonavir (100 mg twice daily). Plasma fluticasone propionate concentrations following fluticasone propionate aqueous nasal spray alone were undetectable (<10 pg/mL) in most subjects, and when concentrations were detectable, peak levels (Cmax) averaged 11.9 pg/mL (range: 10.8 to 14.1 pg/mL) and AUC(0-τ) averaged 8.43 pg•h/mL (range: 4.2 to 18.8 pg•h/mL). Fluticasone propionate Cmax and AUC(0-τ) increased to 318 pg/mL (range: 110 to 648 pg/mL) and 3,102.6 pg•h/mL (range: 1,207.1 to 5,662.0 pg•h/mL), respectively, after coadministration of ritonavir with fluticasone propionate aqueous nasal spray. This significant increase in plasma fluticasone propionate exposure resulted in a significant decrease (86%) in serum cortisol AUC.

Ketoconazole: In a placebo-controlled, crossover trial in 8 healthy adult volunteers, coadministration of a single dose of orally inhaled fluticasone propionate (1,000 mcg) with multiple doses of ketoconazole (200 mg) to steady state resulted in increased plasma fluticasone propionate exposure, a reduction in plasma cortisol AUC, and no effect on urinary excretion of cortisol.

Following orally inhaled fluticasone propionate alone, AUC(2-last) averaged 1.559 ng•h/mL (range: 0.555 to 2.906 ng•h/mL) and AUC(2-∞) averaged 2.269 ng•h/mL (range: 0.836 to 3.707 ng•h/mL). Fluticasone propionate AUC(2-last) and AUC(2-∞) increased to 2.781 ng•h/mL (range: 2.489 to 8.486 ng•h/mL) and 4.317 ng•h/mL (range: 3.256 to 9.408 ng•h/mL), respectively, after coadministration of ketoconazole with orally inhaled fluticasone propionate. This increase in plasma fluticasone propionate concentration resulted in a decrease (45%) in serum cortisol AUC.

Erythromycin: In a multiple-dose drug interaction trial, coadministration of orally inhaled fluticasone propionate (500 mcg twice daily) and erythromycin (333 mg 3 times daily) did not affect fluticasone propionate pharmacokinetics.

13 NONCLINICAL TOXICOLOGY

13.1 Carcinogenesis, Mutagenesis, Impairment of Fertility

Fluticasone propionate demonstrated no tumorigenic potential in mice at oral doses up to 1,000 mcg/kg (approximately 2 and 10 times the MRHDID for adults and children aged 4 to 11 years, respectively, on a mcg/m^2 basis) for 78 weeks or in rats at inhalation doses up to 57 mcg/kg (approximately 0.2 times and approximately equivalent to the MRHDID for adults and children aged 4 to 11 years, respectively, on a mcg/m^2 basis) for 104 weeks.

Fluticasone propionate did not induce gene mutation in prokaryotic or eukaryotic cells in vitro. No significant clastogenic effect was seen in cultured human peripheral lymphocytes in vitro or in the in vivo mouse micronucleus test.

Fertility and reproductive performance were unaffected in male and female rats at subcutaneous doses up to 50 mcg/kg (approximately 0.2 times the MRHDID for adults on a mcg/m^2 basis).

14 CLINICAL STUDIES

14.1 Adult and Adolescent Subjects Aged 12 Years and Older

Four randomized, double-blind, parallel-group, placebo-controlled, U.S. clinical trials were conducted in 1,036 adult and adolescent subjects (aged 12 years and older) with asthma to assess the efficacy and safety of FLOVENT DISKUS in the treatment of asthma. Fixed dosages of 100, 250, and 500 mcg twice daily were compared with placebo to provide information about appropriate dosing to cover a range of asthma severity. Subjects in these trials included those inadequately controlled with bronchodilators alone and those already maintained on daily ICS. All doses were delivered by inhalation of the contents of 1 or 2 blisters from FLOVENT DISKUS twice daily.

Figures 1 through 4 display results of pulmonary function tests (mean percent change from baseline in FEV1 prior to AM dose) for 3 recommended dosages of FLOVENT DISKUS (100, 250, and 500 mcg twice daily) and placebo from the four 12-week trials in adolescents and adults. These trials used predetermined criteria for lack of efficacy (indicators of worsening asthma), resulting in withdrawal of more patients in the placebo group. Therefore, pulmonary function results at Endpoint (the last evaluable FEV1 result, including most patients’ lung function data) are also displayed. Pulmonary function, as determined by percent change from baseline in FEV1 at recommended dosages of FLOVENT DISKUS improved significantly compared with placebo by the first week of treatment, and improvement was maintained for up to 1 year or more.

Figure 1. A 12-Week Clinical Trial Evaluating FLOVENT DISKUS 100 mcg Twice Daily in Adults and Adolescents Receiving Bronchodilators Alone

Figure 2. A 12-Week Clinical Trial Evaluating FLOVENT DISKUS 100 mcg Twice Daily in Adults and Adolescents Receiving Inhaled Corticosteroids

Figure 3. A 12-Week Clinical Trial Evaluating FLOVENT DISKUS 250 mcg Twice Daily in Adults and Adolescents Receiving Inhaled Corticosteroids or Bronchodilators Alone

Figure 4. A 12-Week Clinical Trial Evaluating FLOVENT DISKUS 500 mcg Twice Daily in Adults and Adolescents Receiving Inhaled Corticosteroids or Bronchodilators Alone

In all 4 efficacy trials, measures of pulmonary function (FEV1) were statistically significantly improved as compared with placebo at all twice-daily doses. Subjects on all dosages of FLOVENT DISKUS were also less likely to discontinue study participation due to asthma deterioration (as defined by predetermined criteria for lack of efficacy including lung function and subject-recorded variables such as AM PEF, albuterol use, and nighttime awakenings due to asthma) compared with placebo.

In a clinical trial of 111 subjects with severe asthma requiring chronic oral prednisone therapy (average baseline daily prednisone dose was 14 mg), fluticasone propionate given by inhalation powder at doses of 500 and 1,000 mcg twice daily was evaluated. Both doses enabled a statistically significantly larger percentage of subjects to wean from oral prednisone as compared with placebo (75% of the subjects on 500 mcg twice daily and 89% of the subjects on 1,000 mcg twice daily as compared with 9% of subjects on placebo). Accompanying the reduction in oral corticosteroid use, subjects treated with fluticasone propionate had significantly improved lung function and fewer asthma symptoms as compared with the placebo group.

14.2 Pediatric Subjects Aged 4 to 11 Years

A 12-week, placebo-controlled clinical trial was conducted in 437 pediatric subjects (177 received FLOVENT DISKUS), approximately half of whom were receiving ICS at baseline. In this trial, doses of fluticasone propionate inhalation powder 50 and 100 mcg twice daily significantly improved FEV1 (15% and 18% change from baseline at Endpoint, respectively) compared with placebo (7% change). AM PEF was also significantly improved with doses of fluticasone propionate 50 and 100 mcg twice daily (26% and 27% change from baseline at Endpoint, respectively) compared with placebo (14% change). In this trial, subjects on active treatment were significantly less likely to discontinue treatment due to asthma deterioration (as defined by predetermined criteria for lack of efficacy including lung function and subject-recorded variables such as AM PEF, albuterol use, and nighttime awakenings due to asthma).

Two other 12-week placebo-controlled clinical trials were conducted in 504 pediatric subjects with asthma, approximately half of whom were receiving ICS at baseline. In these trials, FLOVENT DISKUS was efficacious at doses of 50 and 100 mcg twice daily when compared with placebo on major endpoints including lung function and symptom scores. Pulmonary function improved significantly compared with placebo by the first week of treatment, and subjects treated with FLOVENT DISKUS were also less likely to discontinue trial participation due to asthma deterioration. One hundred ninety-two (192) subjects received FLOVENT DISKUS for up to 1 year during an open-label extension. Data from this open-label extension suggested that lung function improvements could be maintained up to 1 year.

16 HOW SUPPLIED/STORAGE AND HANDLING

Product: 50090-1245

NDC: 50090-1245-0 60 POWDER, METERED in a INHALER / 1 in a CARTON

17 PATIENT COUNSELING INFORMATION

Advise the patient to read the FDA-approved patient labeling (Patient Information and Instructions for Use).

Local Effects

Inform patients that localized infections with Candida albicans occurred in the mouth and pharynx in some patients. If oropharyngeal candidiasis develops, treat it with appropriate local or systemic (i.e., oral) antifungal therapy while still continuing therapy with FLOVENT DISKUS, but at times therapy with FLOVENT DISKUS may need to be temporarily interrupted under close medical supervision. Advise patients to rinse the mouth with water without swallowing after inhalation to help reduce the risk of thrush.

Status Asthmaticus and Acute Asthma Symptoms

Inform patients that FLOVENT DISKUS is not a bronchodilator and is not intended for use as rescue medicine for acute asthma exacerbations. Advise patients to treat acute asthma symptoms with an inhaled, short-acting beta2-agonist such as albuterol. Instruct patients to contact their physicians immediately if there is deterioration of their asthma.

Immunosuppression

Warn patients who are on immunosuppressant doses of corticosteroids to avoid exposure to chickenpox or measles and, if exposed, to consult their physicians without delay. Inform patients of potential worsening of existing tuberculosis; fungal, bacterial, viral, or parasitic infections; or ocular herpes simplex.

Hypercorticism and Adrenal Suppression

Advise patients that FLOVENT DISKUS may cause systemic corticosteroid effects of hypercorticism and adrenal suppression. Additionally, inform patients that deaths due to adrenal insufficiency have occurred during and after transfer from systemic corticosteroids. Patients should taper slowly from systemic corticosteroids if transferring to FLOVENT DISKUS.

Immediate Hypersensitivity Reactions

Advise patients that immediate hypersensitivity reactions (e.g., urticaria, angioedema, rash, bronchospasm, hypotension), including anaphylaxis, may occur after administration of FLOVENT DISKUS. Patients should discontinue FLOVENT DISKUS if such reactions occur. There have been reports of anaphylactic reactions in patients with severe milk protein allergy after inhalation of powder products containing lactose; therefore, patients with severe milk protein allergy should not take FLOVENT DISKUS.

Reduction in Bone Mineral Density

Advise patients who are at an increased risk for decreased BMD that the use of corticosteroids may pose an additional risk.

Reduced Growth Velocity

Inform patients that orally inhaled corticosteroids, including FLOVENT DISKUS, may cause a reduction in growth velocity when administered to pediatric patients. Physicians should closely follow the growth of children and adolescents taking corticosteroids by any route.

Glaucoma and Cataracts

Advise patients that long-term use of ICS may increase the risk of some eye problems (cataracts or glaucoma); consider regular eye examinations.

Use Daily for Best Effect

Patients should use FLOVENT DISKUS at regular intervals as directed. Individual patients will experience a variable time to onset and degree of symptom relief and the full benefit may not be achieved until treatment has been administered for 1 to 2 weeks or longer. Patients should not increase the prescribed dosage but should contact their physicians if symptoms do not improve or if the condition worsens. Instruct patients not to stop use of FLOVENT DISKUS abruptly. Patients should contact their physicians immediately if they discontinue use of FLOVENT DISKUS.

Trademarks are owned by or licensed to the GSK group of companies.

GlaxoSmithKline

Durham, NC 27701

©2023 GSK group of companies or its licensor.

FLD:16PI

PATIENT INFORMATION

FLOVENT DISKUS (FLO vent DISK us)

(fluticasone propionate inhalation powder)

for oral inhalation use

What is FLOVENT DISKUS?

FLOVENT DISKUS is a prescription inhaled corticosteroid (ICS) medicine used for the long-term treatment of asthma in people aged 4 years and older.

- ICS medicines such as fluticasone propionate help to decrease inflammation in the lungs. Inflammation in the lungs can lead to breathing problems.
- FLOVENT DISKUS is not used to relieve sudden breathing problems and will not replace a rescue inhaler.
- It is not known if FLOVENT DISKUS is safe and effective in children younger than 4 years of age.

Do not use FLOVENT DISKUS:

- to relieve sudden breathing problems.
- as a rescue inhaler.
- if you have a severe allergy to milk proteins. Ask your healthcare provider if you are not sure.
- if you are allergic to fluticasone propionate.

Before using FLOVENT DISKUS, tell your healthcare provider about all of your medical conditions, including if you:

- have liver problems.
- have weak bones (osteoporosis).
- have an immune system problem.
- have or have had eye problems, such as glaucoma, increased pressure in your eye, cataracts, or other changes in vision.
- are allergic to milk proteins.
- have any type of viral, bacterial, or fungal infection.
- are exposed to chickenpox or measles.
- are pregnant or plan to become pregnant. It is not known if FLOVENT DISKUS may harm your unborn baby.
- are breastfeeding. It is not known if the medicine in FLOVENT DISKUS passes into your milk and if it can harm your baby.

Tell your healthcare provider about all the medicines you take, including prescription and over-the-counter medicines, vitamins, and herbal supplements. FLOVENT DISKUS and certain other medicines may interact with each other. This may cause serious side effects. Especially tell your healthcare provider if you take antifungal or anti-HIV medicines.

Know the medicines you take. Keep a list of them to show your healthcare provider and pharmacist when you get a new medicine.

How should I use FLOVENT DISKUS?

Read the step-by-step instructions for using FLOVENT DISKUS at the end of this Patient Information.

- Do not use FLOVENT DISKUS unless your healthcare provider has taught you how to use the inhaler and you understand how to use it correctly.
- Children should use FLOVENT DISKUS with an adult’s help, as instructed by the child’s healthcare provider.
- FLOVENT DISKUS comes in 3 different strengths. Your healthcare provider prescribed the strength that is best for you.
- Use FLOVENT DISKUS exactly as your healthcare provider tells you to use it. Do not use FLOVENT DISKUS more often than prescribed.
- It may take 1 to 2 weeks or longer after you start FLOVENT DISKUS for your asthma symptoms to get better. You must use FLOVENT DISKUS regularly.
- Do not stop using FLOVENT DISKUS, even if you are feeling better, unless your healthcare provider tells you to.
- If you miss a dose of FLOVENT DISKUS, just skip that dose. Take your next dose at your usual time. Do not take 2 doses at 1 time.
- FLOVENT DISKUS does not relieve sudden breathing problems. Always have a rescue inhaler with you to treat sudden symptoms. If you do not have a rescue inhaler, call your healthcare provider to have one prescribed for you.
- Rinse your mouth with water without swallowing after each dose of FLOVENT DISKUS. This will help lessen the chance of getting a yeast infection (thrush) in your mouth and throat.
- Call your healthcare provider or get medical care right away if:
- your breathing problems get worse.
- you need to use your rescue inhaler more often than usual.
- your rescue inhaler does not work as well to relieve your symptoms.
- you need to use 4 or more inhalations of your rescue inhaler in 24 hours for 2 or more days in a row.
- you use 1 whole canister of your rescue inhaler in 8 weeks.
- your peak flow meter results decrease. Your healthcare provider will tell you the numbers that are right for you.

What are the possible side effects of FLOVENT DISKUS?

FLOVENT DISKUS can cause serious side effects, including:

- fungal infection in your mouth or throat (thrush). Rinse your mouth with water without swallowing after using FLOVENT DISKUS to help reduce your chance of getting thrush.
- weakened immune system and increased chance of getting infections (immunosuppression).
- reduced adrenal function (adrenal insufficiency). Adrenal insufficiency is a condition where the adrenal glands do not make enough steroid hormones. This can happen when you stop taking oral corticosteroid medicines (such as prednisone) and start taking a medicine containing an inhaled steroid (such as FLOVENT DISKUS). During this transition period, when your body is under stress such as from fever, trauma (such as a car accident), infection, or surgery, adrenal insufficiency can get worse and may cause death.
Symptoms of adrenal insufficiency include:

ο feeling tired ο nausea and vomiting

ο lack of energy ο low blood pressure (hypotension)

ο weakness

- serious allergic reactions. Call your healthcare provider or get emergency medical care if you get any of the following symptoms of a serious allergic reaction:

ο rash ο swelling of your face, mouth and tongue

ο hives ο breathing problems

- bone thinning or weakness (osteoporosis).
- slowed growth in children. Your child’s growth should be checked regularly by the healthcare provider while using FLOVENT DISKUS.
- eye problems including glaucoma, increased pressure in your eye, cataracts, or other changes in vision. You should have regular eye exams while using FLOVENT DISKUS.
- increased wheezing (bronchospasm). Increased wheezing can happen right away after using FLOVENT DISKUS. Always have a rescue inhaler with you to treat sudden wheezing.

Common side effects of FLOVENT DISKUS include:

• upper respiratory tract infection • fever • nose irritation

• throat irritation • headache • upset stomach

• nausea and vomiting • sinus irritation

• persistent cough • cough

These are not all the possible side effects of FLOVENT DISKUS.

Call your doctor for medical advice about side effects. You may report side effects to FDA at 1-800-FDA-1088.

How should I store FLOVENT DISKUS?

- Store FLOVENT DISKUS at room temperature between 68°F and 77°F (20°C and 25°C). Keep in a dry place away from heat and sunlight.
- Store FLOVENT DISKUS in the unopened foil pouch and only open when ready for use.
- Safely throw away FLOVENT DISKUS 50 mcg in the trash 6 weeks after you open the foil pouch or when the counter reads 0, whichever comes first.
- Safely throw away FLOVENT DISKUS 100 mcg and FLOVENT DISKUS 250 mcg in the trash 2 months after you open the foil pouch or when the counter reads 0, whichever comes first.

Keep FLOVENT DISKUS and all medicines out of the reach of children.

General information about the safe and effective use of FLOVENT DISKUS.

Medicines are sometimes prescribed for purposes other than those listed in a Patient Information leaflet. Do not use FLOVENT DISKUS for a condition for which it was not prescribed. Do not give FLOVENT DISKUS to other people, even if they have the same symptoms that you have. It may harm them.

You can ask your healthcare provider or pharmacist for information about FLOVENT DISKUS that is written for health professionals.

What are the ingredients in FLOVENT DISKUS?

Active ingredient: fluticasone propionate

Inactive ingredient: lactose monohydrate (contains milk proteins)

For more information about FLOVENT DISKUS, call 1-888-825-5249.

Trademarks are owned by or licensed to the GSK group of companies.

GlaxoSmithKline, Durham, NC 27701

©2023 GSK group of companies or its licensor.

FLD:11PIL

This Patient Information has been approved by the U.S. Food and Drug Administration Revised: August 2023

INSTRUCTIONS FOR USE

FLOVENT DISKUS (FLO vent DISK us)

(fluticasone propionate inhalation powder)

for oral inhalation use

Your FLOVENT DISKUS inhaler

Figure A

Read this information before you start using your FLOVENT DISKUS inhaler:

- Take FLOVENT DISKUS out of the foil pouch just before you use it for the first time. Safely throw away the pouch. The DISKUS will be in the closed position.
- Write the date you opened the foil pouch in the first blank line on the label. See Figure A.
- Write the “use by” date in the second blank line on the label. See Figure A. If you are using FLOVENT DISKUS 50 mcg, that date is 6 weeks after the date you wrote in the first line. If you are using FLOVENT DISKUS 100 mcg or 250 mcg, that date is 2 months after the date you wrote in the first line.
- The counter should read 60.

How to use your FLOVENT DISKUS inhaler

Follow these steps every time you use FLOVENT DISKUS.

Step 1. Open your FLOVENT DISKUS.

- Hold the DISKUS in your left hand and place the thumb of your right hand in the thumb grip. Push the thumb grip away from you as far as it will go until the mouthpiece shows and snaps into place. See Figure B.

Figure B

Step 2. Slide the lever until you hear it click.

- Hold the DISKUS in a level, flat position with the mouthpiece towards you. Slide the lever away from the mouthpiece as far as it will go until it clicks. See Figure C.

Figure C

- The number on the counter will count down by 1. The DISKUS is now ready to use.

Follow the instructions below so you will not accidentally waste an inhalation of medicine:

- Do not close the DISKUS.
- Do not tilt the DISKUS.
- Do not move the lever on the DISKUS.

Step 3. Inhale your medicine.

- Before you breathe in your medicine from the DISKUS, breathe out (exhale) as long as you can while you hold the DISKUS level and away from your mouth. See Figure D. Do not breathe into the mouthpiece.

Figure D

- Put the mouthpiece to your lips. See Figure E. Breathe in quickly and deeply through the DISKUS. Do not breathe in through your nose.

Figure E

- Remove the DISKUS from your mouth and hold your breath for about 10 seconds, or for as long as is comfortable for you.
- Breathe out slowly as long as you can. See Figure D.
- The DISKUS delivers your medicine as a very fine powder that you may or may not taste or feel. Do not take an extra inhalation from the DISKUS even if you do not taste or feel the medicine.

Step 4. Close the DISKUS.

- Place your thumb in the thumb grip and slide it back towards you as far as it will go. See Figure F. Make sure the DISKUS clicks shut and you cannot see the mouthpiece.

Figure F

If your healthcare provider has told you to take more than 1 inhalation of FLOVENT DISKUS per dose, repeat Steps 1 through 4.

Step 5. Rinse your mouth.

- Rinse your mouth with water after breathing in the medicine. Spit out the water. Do not swallow it. See Figure G.

Figure G

When you are ready to take your next scheduled dose in about 12 hours, repeat Steps 1 through 5.

When should you get a refill?

The counter on top of the DISKUS shows you how many doses are left. After you have taken 55 doses, the numbers 5 to 0 will show in red. See Figure H. These numbers warn you there are only a few doses left and are a reminder to get a refill.

Figure H

For correct use of the DISKUS, remember:

- Always use the DISKUS in a level, flat position.
- Make sure the lever firmly clicks into place.
- Hold your breath for about 10 seconds after inhaling. Then breathe out fully.
- After each dose, rinse your mouth with water and spit it out. Do not swallow the water.
- Do not take an extra dose, even if you did not taste or feel the powder.
- Do not take the DISKUS apart.
- Do not wash the DISKUS.
- Always keep the DISKUS in a dry place.
- Do not use the DISKUS with a spacer device.

For more information about FLOVENT DISKUS or how to use your inhaler, call 1-888-825-5249.

Trademarks are owned by or licensed to the GSK group of companies.

GlaxoSmithKline, Durham, NC 27701

©2023 GSK group of companies or its licensor.

FLD:7IFU

This Instructions for Use has been approved by the U.S. Food and Drug Administration Revised: August 2023